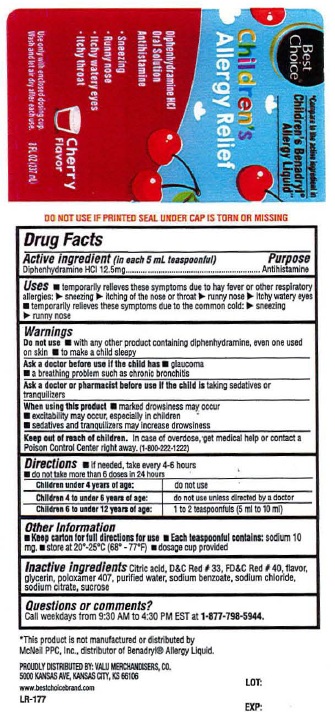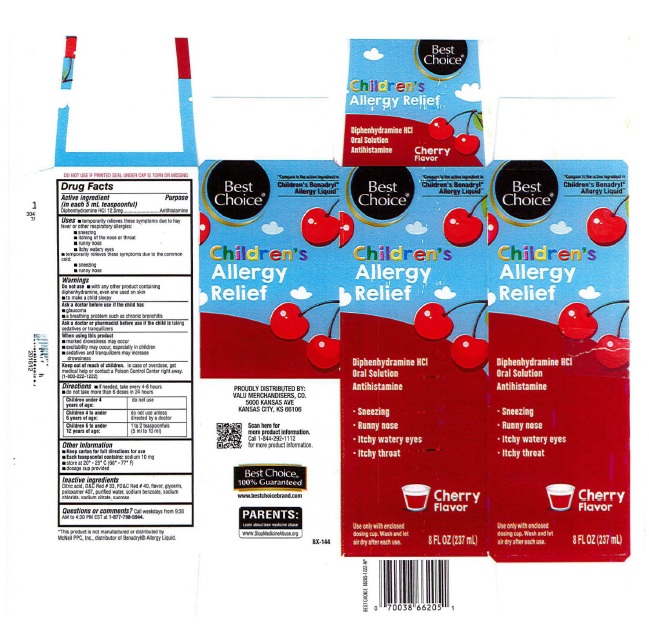 DRUG LABEL: Childrens Allergy Relief
NDC: 63941-505 | Form: SOLUTION
Manufacturer: Best Choice
Category: otc | Type: HUMAN OTC DRUG LABEL
Date: 20250122

ACTIVE INGREDIENTS: DIPHENHYDRAMINE HCL 12.5 mg/5 mL
INACTIVE INGREDIENTS: CITRIC ACID; D&C RED NO. 33; FD&C RED NO. 40; GLYCERIN; POLOXAMER 407; WATER; SODIUM BENZOATE; SODIUM CHLORIDE; SODIUM CITRATE; SUCROSE

Best Choice® Children's Allergy Relief

Drug Facts

Active ingredients

(in each 5 mL teaspoonful)
Diphenhydramine HCl 12.5 mg

Purpose

Antihistamine

Uses

temporarily relieves these symptoms due to hay fever or other respiratory allergies:
■ sneezing
■ itching of the nose or throat
■ runny nose
■ itchy watery eyes
■temporarily relieves these symptoms due to the common cold:
■ sneezing
■ runny nose

Warnings

Do not use
■ with any other product containing diphenhydramine, even one used on skin
■ to make a child sleepy

Ask a doctor before use if the child has
■ glaucoma
■ a breathing problem such as chronic bronchitis

Ask a doctor or pharmacist before use if the child is taking sedatives or tranquillizers

When using this product
■ marked drowsiness may occur
■ excitability may occur, especially in children
■ sedatives and tranquilizers may increase drowsiness

Keep out of reach of children. In case of overdose, get
medical help or contact a Poison Control Center right
away, (1-800-222-1222)

Directions
■ if needed, take every 4-6 hours
■ do not take more than 6 doses in 24-hours

children under 4 years of age | Do not use
children 4 to under 6 years of age | Do not use unless directed by a doctor
children 6 to under 12 years of age | 1 to 2 teaspoonfuls (5 ml to 10 ml)

Other information
■ Keep carton for full directions for use
■ Each teaspoonful contains: sodium 10 mg
■ store at 20 - 25º C (68 - 77" F)
■ dosage cup provided

Inactive ingredients

citric acid, D&C red # 33, FD&C Red #40, flavor, glycerin, poloxamer 407, purified water, sodium benzoate, sodium
chloride, sodium citrate, sucrose

QUESTIONS

Questions? Call weekdays from 9:30 AM to 4:30 PM EST at 1-877-798-5944

-----------

Product Label: Best Choice® Children's Allergy Relief

Best Choice®

Children's Allergy Relief

Diphenhydramine HCl

Oral Solution

Antihistamine

Cherry Flavor

8 FL OZ (237 mL)

* This product is not manufactured or distributed by McNeil PPC, Inc., distributor of Benadryl® Allergy Liquid.

PROUDLY DISTRIBUTED BY: VALU MERCHANDISERS, CO.
5000 KANSAS AVE, KANSAS CITY, KS 66106

Carton

Bottle

res